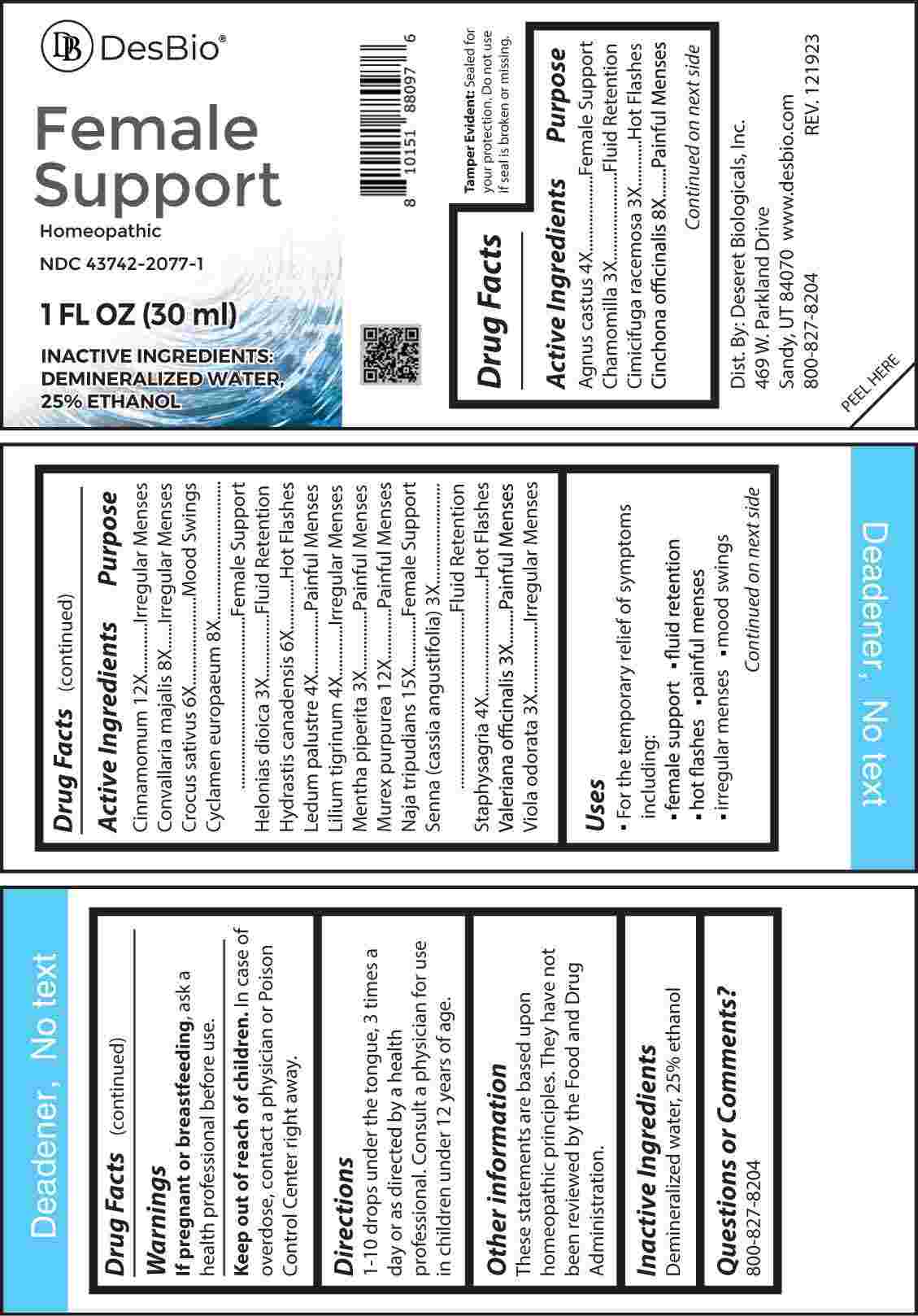 DRUG LABEL: Female Support
NDC: 43742-2077 | Form: LIQUID
Manufacturer: Deseret Biologicals, Inc.
Category: homeopathic | Type: HUMAN OTC DRUG LABEL
Date: 20240404

ACTIVE INGREDIENTS: MATRICARIA CHAMOMILLA WHOLE 3 [hp_X]/1 mL; BLACK COHOSH 3 [hp_X]/1 mL; CHAMAELIRIUM LUTEUM ROOT 3 [hp_X]/1 mL; MENTHA X PIPERITA WHOLE 3 [hp_X]/1 mL; SENNA LEAF 3 [hp_X]/1 mL; VALERIAN 3 [hp_X]/1 mL; VIOLA ODORATA WHOLE 3 [hp_X]/1 mL; CHASTE TREE FRUIT 4 [hp_X]/1 mL; RHODODENDRON TOMENTOSUM LEAFY TWIG 4 [hp_X]/1 mL; LILIUM LANCIFOLIUM WHOLE FLOWERING 4 [hp_X]/1 mL; DELPHINIUM STAPHISAGRIA SEED 4 [hp_X]/1 mL; SAFFRON 6 [hp_X]/1 mL; GOLDENSEAL 6 [hp_X]/1 mL; CINCHONA OFFICINALIS BARK 8 [hp_X]/1 mL; CONVALLARIA MAJALIS 8 [hp_X]/1 mL; CYCLAMEN PURPURASCENS TUBER 8 [hp_X]/1 mL; CINNAMON 12 [hp_X]/1 mL; HEXAPLEX TRUNCULUS HYPOBRANCHIAL GLAND JUICE 12 [hp_X]/1 mL; NAJA NAJA VENOM 15 [hp_X]/1 mL
INACTIVE INGREDIENTS: WATER; ALCOHOL

DRUG FACTS:

ACTIVE INGREDIENTS:

Agnus Castus 4X, Chamomilla 3X, Cimicifuga Racemosa 3X, Cinchona Officinalis 8X, Cinnamomum 12X, Convallaria Majalis 8X, Crocus Sativus 6X, Cyclamen Europaeum 8X, Helonias Dioica 3X, Hydrastis Canadensis 6X, Ledum Palustre 4X, Lilium Tigrinum 4X, Mentha Piperita 3X, Murex Purpurea 12X, Naja Tripudians 15X, Senna (Cassia Angustifolia) 3X, Staphysagria 4X, Valeriana Officinalis 3X, Viola Odorata 3X.

PURPOSE:

Agnus Castus – Female Support, Chamomilla – Fluid Retention, Cimicifuga Racemosa – Hot Flashes, Cinchona Officinalis – Painful Menses, Cinnamomum – Irregular Menses, Convallaria Majalis – Irregular Menses, Crocus Sativus – Mood Swings, Cyclamen Europaeum – Female Support, Helonias Dioica – Fluid Retention, Hydrastis Canadensis – Hot Flashes, Ledum Palustre – Painful Menses, Lilium Tigrinum – Irregular Menses, Mentha Piperita – Painful Menses, Murex Purpurea – Painful Menses, Naja Tripudians – Female Support, Senna (Cassia Angustifolia) – Fluid Retention, Staphysagria – Hot Flashes, Valeriana Officinalis – Painful Menses, Viola Odorata – Irregular Menses

USES:

• For the temporary relief of symptoms including:

• female support • fluid retention • hot flashes

• painful menses • irregular menses • mood swings

These statements are based upon homeopathic principles. They have not been reviewed by the Food and Drug Administration.

WARNINGS:

If pregnant or breast-feeding, ask a health professional before use.

Keep out of reach of children. In case of overdose, contact a physician or Poison Control Center right away.

Tamper Evident: Sealed for your protection. Do not use if seal is broken or missing.

KEEP OUT OF REACH OF CHILDREN:

In case of overdose, contact a physician or Poison Control Center right away.

DIRECTIONS:

1-10 drops under the tongue, 3 times a day or as directed by a health professional. Consult a physician for use in children under 12 years of age.

INACTIVE INGREDIENTS:

Demineralized water, 25% ethanol

QUESTIONS:

Dist. By: Deseret Biologicals, Inc.

469 W. Parkland Drive

Sandy, UT 84070

www.desbio.com

800-827-8204

PACKAGE LABEL DISPLAY:

Des Bio

Female Support

Homeopathic

NDC 43742-2077-1

1 FL OZ (30ml)